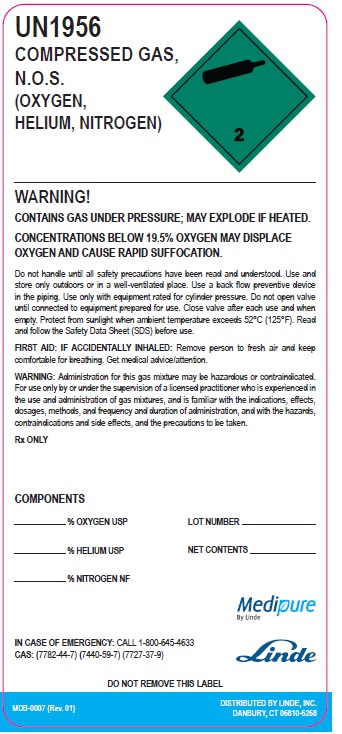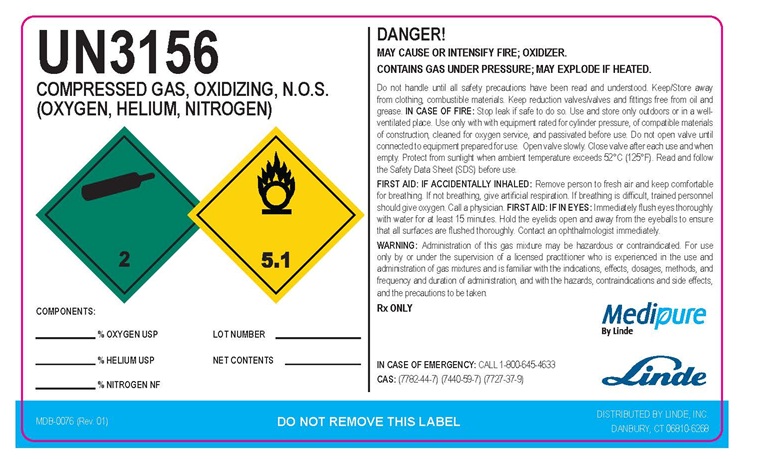 DRUG LABEL: Helium Oxygen Nitrogen mixture
NDC: 59579-010 | Form: GAS
Manufacturer: Linde Gas & Equipment Inc.
Category: prescription | Type: HUMAN PRESCRIPTION DRUG LABEL
Date: 20251230

ACTIVE INGREDIENTS: HELIUM 200 mL/1 L; OXYGEN 500 mL/1 L; NITROGEN 300 mL/1 L

Helium Oxygen Nitrogen Mixture

Oxygen, Helium, Nitrogen Mix

UN1956

COMPRESSED GAS,

N.O.S.

(OXYGEN,

HELIUM, NITROGEN)

WARNING!

CONTAINS GAS UNDER PRESSURE; MAY EXPLODE IF HEATED.
CONCENTRATIONS BELOW 19.5% OXYGEN MAY DISPLACE OXYGEN AND CAUSE RAPID SUFFOCATION.

Do not handle until all safety precautions have been read and understood. Use and store only outdoors or in a well-ventilated place. Use a back flow preventive device in the piping. Use only with equipment rated for cylinder pressure. Do not open valve until connected to equipment prepared for use. Close valve after each use and when empty. Protect from sunlight when ambient temperature exceeds 52°C (125°F). Read and follow the Safety Data Sheet (SDS) before use.

FIRST AID: IF ACCIDENTALLY INHALED: Remove person to fresh air and keep comfortable for breathing. Get medical advice/attention.

WARNING: Administration for this gas mixture may be hazardous or contraindicated. For use only by or under the supervision of a licensed practitioner who is experienced in the use and administration of gas mixtures, and is familiar with the indications, effects, dosages, methods, and frequency and duration of administration, and with the hazards, contraindications and side effects, and the precautions to be taken.

Rx ONLY

COMPONENTS

_____% OXYGEN USP LOT NUMBER_____________
_____% HELIUM USP NET CONTENTS___________
_____% NITROGEN NF

IN CASE OF EMERGENCY: CALL 1-800-645-4633

CAS: (7782-44-7) (7440-59-7) (7727-37-9)

DO NOT REMOVE THIS LABEL

MDB-0007 (Rev. 01)
DISTRIBUTED BY LINDE, INC.
DANBURY, CT 06810-6268

Oxygen, Helium, Nitrogen Mix

UN3156

COMPRESSED GAS,

OXIDIZING N.O.S.

(OXYGEN, HELIUM, NITROGEN)

COMPONENTS

_____% OXYGEN USP LOT NUMBER_____________
_____% HELIUM USP NET CONTENTS___________
_____% NITROGEN NF

DANGER!

MAY CAUSE OR INTENSIFY FIRE; OXIDIZER.

GAS UNDER PRESSURE; MAY EXPLODE IF HEATED.

Do not handle until all safety precautions have been read and understood. Keep/Store away from clothing, combustible materials. Keep reduction valves/valves and fittings free from oil and grease. IN CASE OF FIRE: Stop leak if safe to do so. Use and store only outdoors or in a well-ventilated place. Use only with with equipment rated for cylinder pressure, of compatible materials of construction, cleaned for oxygen service, and passivated before use. Do not open valve until connected to equipment prepared for use. Open valve slowly. Close valve after each use and when empty. Protect from sunlight when ambient temperature exceeds 52°C (125°F). Read and follow the Safety Data Sheet (SDS) before use.

FIRST AID: IF ACCIDENTALLY INHALED: Remove person to fresh air and keep comfortable for breathing. If not breathing, give artificial respiration. If breathing is difficult, trained personnel should give oxygen. Call a physician. FIRST AID: IF IN EYES: Immediately flush eyes thoroughly with water for at least 15 minutes. Hold the eyelids open and away from the eyeballs to ensure that all surfaces are flushed thoroughly. Contact an ophthalmologist immediately.

WARNING: Administration of this gas mixture may be hazardous or contraindicated. For use only by or under the supervision of a licensed practitioner who is experienced in the use and administration of gas mixtures and is familiar with the indications, effects, dosages, methods, and frequency and duration of administration, and with the hazards, contraindications and side effects, and the precautions to be taken.
Rx ONLY

IN CASE OF EMERGENCY: CALL 1-800-645-4633

CAS: (7782-44-7) (7440-59-7) (7727-37-9)

MDB-0076 (Rev. 01)

DO NOT REMOVE THIS LABEL

DISTRIBUTED BY LINDE, INC.
DANBURY, CT 06810-6268